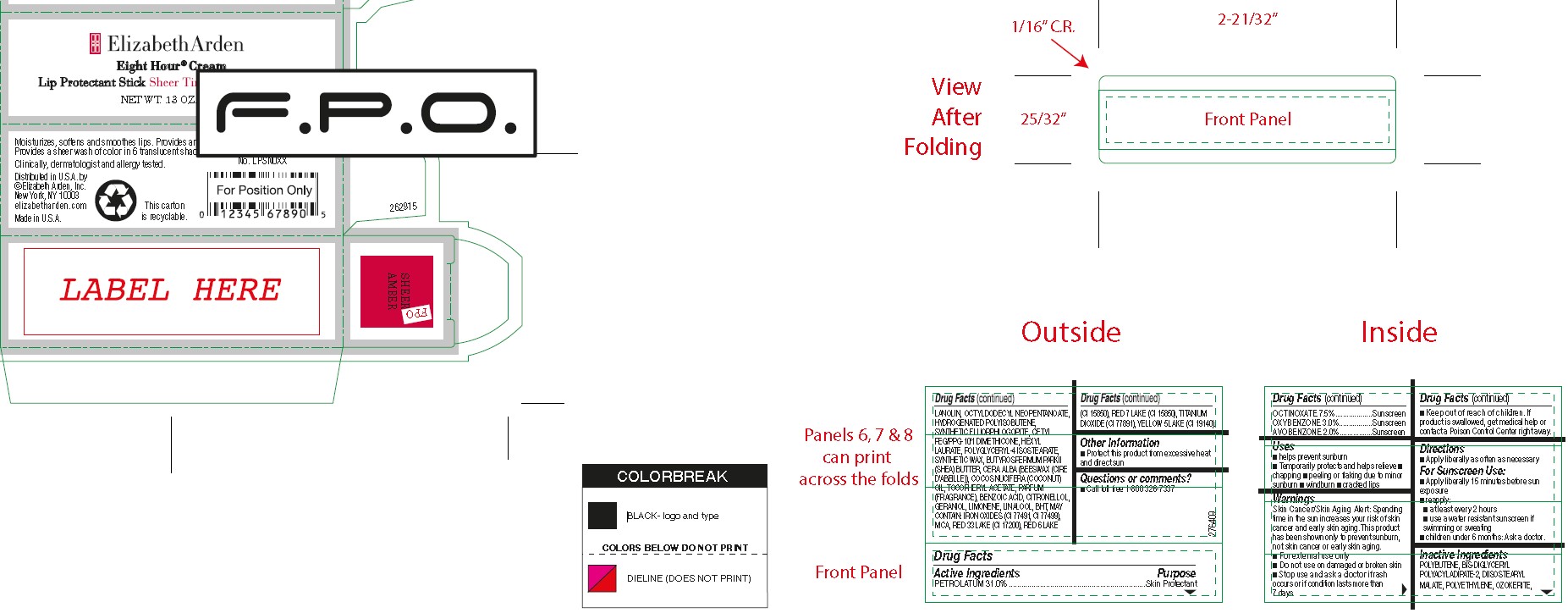 DRUG LABEL: EA EIGHT HR LIP SHEER TINTS
NDC: 10967-674 | Form: LIPSTICK
Manufacturer: REVLON
Category: otc | Type: HUMAN OTC DRUG LABEL
Date: 20240112

ACTIVE INGREDIENTS: PADIMATE O 8 mg/1 g; PETROLATUM 30.2 mg/1 g; OXYBENZONE 3 mg/1 g
INACTIVE INGREDIENTS: CETYL ACETATE; TITANIUM DIOXIDE; FD&C YELLOW NO. 5; CETYL LACTATE; BUTYLATED HYDROXYTOLUENE; CAPRYLYL GLYCOL; PHENOXYETHANOL; FERRIC OXIDE YELLOW; SOYBEAN OIL; HIGH DENSITY POLYETHYLENE; LANOLIN OIL; FD&C YELLOW NO. 6; MYRISTYL LACTATE; CARNAUBA WAX; GLYCERYL ROSINATE; TOCOPHEROL; .BETA.-CITRONELLOL, (R)-; LIMONENE, (+)-; CORN OIL; CASTOR OIL; WHITE WAX; D&C RED NO. 6; D&C RED NO. 7; MICA; CERESIN; CITRAL; LINALOOL, (+/-)-; FERROSOFERRIC OXIDE; D&C RED NO. 28; FERRIC OXIDE RED; CANDELILLA WAX; ACETYLATED LANOLIN ALCOHOLS; MICROCRYSTALLINE WAX; GERANIOL

EA 8Hr Lip Protectant Stick Sheer Tints

ACTIVE INGREDIENTS

OCTINOXATE 7.5%...................Sunscreen
OXYBENZONE 3.0%.................Sunscreen
AVOBENZONE 2.0%.................Sunscreen

INACTIVE INGREDIENTS

POLYBUTENE, BIS-DIGLYCERYL POLYACYLADIPATE-2, DIISOSTEARYL MALATE, POLYETHYLENE, OZOKERITE, LANOLIN, OCTYLDODECYL NEOPENTANOATE, HYDROGENATED POLYISOBUTENE, SYNTHETIC FLUORPHLOGOPITE, CETYL
PEG/PPG-10/1 DIMETHICONE, HEXYL LAURATE, POLYGLYCERYL-4 ISOSTEARATE, SYNTHETIC WAX, BUTYROSPERMUM PARKII (SHEA) BUTTER, CERA ALBA (BEESWAX (CIRE D’ABEILLE)), COCOS NUCIFERA (COCONUT) OIL, TOCOPHERYL ACETATE, PARFUM (FRAGRANCE), BENZOIC ACID, CITRONELLOL, GERANIOL, LIMONENE, LINALOOL, BHT,

MAY CONTAIN: IRON OXIDES (CI 77491, CI 77499), MICA, RED 33 LAKE (CI 17200), RED 6 LAKE (CI 15850), RED 7 LAKE (CI 15850), TITANIUM DIOXIDE (CI 77891), YELLOW 5 LAKE (CI 19140).

USES

■ helps prevent sunburn
■ Temporarily protects and helps relieve

■ chapping

■ peeling or flaking due to minor sunburn

■ windburn

■ cracked lips

WARNINGS

Skin Cancer/Skin Aging Alert: Spending time in the sun increases your risk of skin cancer and early skin aging. This product has been shown only to prevent sunburn, not skin cancer or early skin aging.
■ For external use only
■ Do not use on damaged or broken skin
■ Stop use and ask a doctor if rash occurs or

■ Keep out of reach of children. If product is swallowed, get medical help or contact a Poison Control Center right away.

DIRECTIONS

■ Apply liberally as often as necessary

For Sunscreen Use:
■ Apply liberally 15 minutes before sun exposure
■ reapply:
■ at least every 2 hours
■ use a water resistant sunscreen if swimming or sweating
■ children under 6 months: Ask a doctor.

DOSAGE AND ADMINISTRATION

As needed

INDICATIONS AND USAGE

- Helps prevent sunburn
- Temporarily protects and helps relieve
  - peeling or flaking due to minor sunburn
  - windburn
  - cracked lips

Keep out of reach of children. If product is swallowed, get medical help or contact a Poison Control Center right away.

PURPOSE

Sunscreen

Skin Protectant